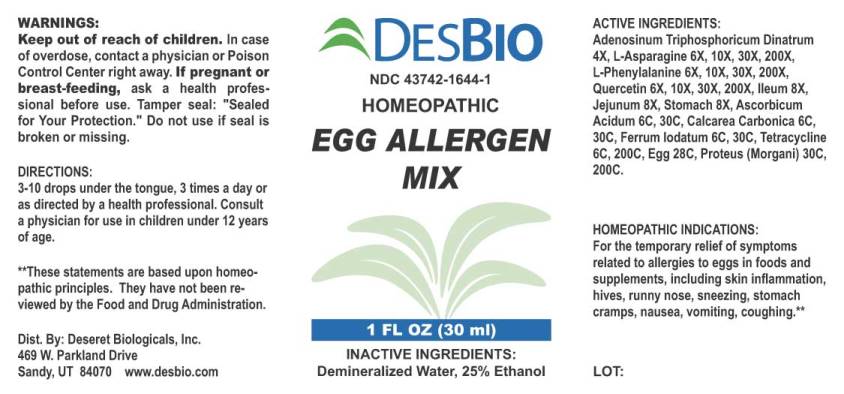 DRUG LABEL: Egg Allergen Mix
NDC: 43742-1644 | Form: LIQUID
Manufacturer: Deseret Biologicals, Inc.
Category: homeopathic | Type: HUMAN OTC DRUG LABEL
Date: 20240116

ACTIVE INGREDIENTS: ADENOSINE TRIPHOSPHATE DISODIUM 4 [hp_X]/1 mL; ASPARAGINE MONOHYDRATE 6 [hp_X]/1 mL; PHENYLALANINE 6 [hp_X]/1 mL; QUERCETIN 6 [hp_X]/1 mL; SUS SCROFA ILEUM 8 [hp_X]/1 mL; SUS SCROFA JEJUNUM 8 [hp_X]/1 mL; SUS SCROFA STOMACH 8 [hp_X]/1 mL; ASCORBIC ACID 6 [hp_C]/1 mL; OYSTER SHELL CALCIUM CARBONATE, CRUDE 6 [hp_C]/1 mL; FERROUS IODIDE 6 [hp_C]/1 mL; TETRACYCLINE 6 [hp_C]/1 mL; EGG 28 [hp_C]/1 mL; PROTEUS MORGANII 30 [hp_C]/1 mL
INACTIVE INGREDIENTS: WATER; ALCOHOL

DRUG FACTS:

ACTIVE INGREDIENTS:

Adenosinum Triphosphoricum Dinatrum 4X, L-Asparagine (Monohydrate) 6X, 10X, 30X, 200X, L-Phenylalanine 6X, 10X, 30X, 200X, Quercetin 6X, 10X, 30X, 200X, Ileum (Suis) 8X, Jejunum (Suis) 8X, Stomach (Suis) 8X, Ascorbicum Acidum 6C, 30C, Calcarea Carbonica 6C, 30C, Ferrum Iodatum 6C, 30C, Tetracycline 6C, 30C, Egg (Hen Whole) 28C, Proteus (Morgani) 30C, 200C.

INDICATIONS:

For the temporary relief of symptoms related to allergies to eggs in foods and supplements, including skin inflammation, hives, runny nose, sneezing, stomach cramps, nausea, vomiting, coughing.**

**These statements are based upon homeopathic principles. They have not been reviewed by the Food and Drug Administration.

WARNINGS:

Keep out of reach of children. In case of overdose, contact a physician or Poison Control Center right away.

If pregnant or breast-feeding, ask a health professional before use.

Tamper seal: "Sealed for Your Protection." Do not use if seal is broken or missing.

Keep out of reach of children. In case of overdose, get medical help or contact a Poison Control Center right away.

DIRECTIONS:

3-10 drops under the tongue, 3 times a day or as directed by a health professional. Consult a physician for use in children under 12 years of age.

INDICATIONS:

For the temporary relief of symptoms related to allergies to eggs in foods and supplements, including skin inflammation, hives, runny nose, sneezing, stomach cramps, nausea, vomiting, coughing.**

**These statements are based upon homeopathic principles. They have not been reviewed by the Food and Drug Administration.

INACTIVE INGREDIENTS:

Demineralized Water, 25% Ethanol

QUESTIONS:

Dist. By: Deseret Biologicals, Inc.

469 W. Parkland Drive

Sandy, UT 84070 www.desbio.com

PACKAGE LABEL DISPLAY:

DESBIO

NDC 43742-1644-1

HOMEOPATHIC

EGG ALLERGEN

MIX

1 FL OZ (30 ml)